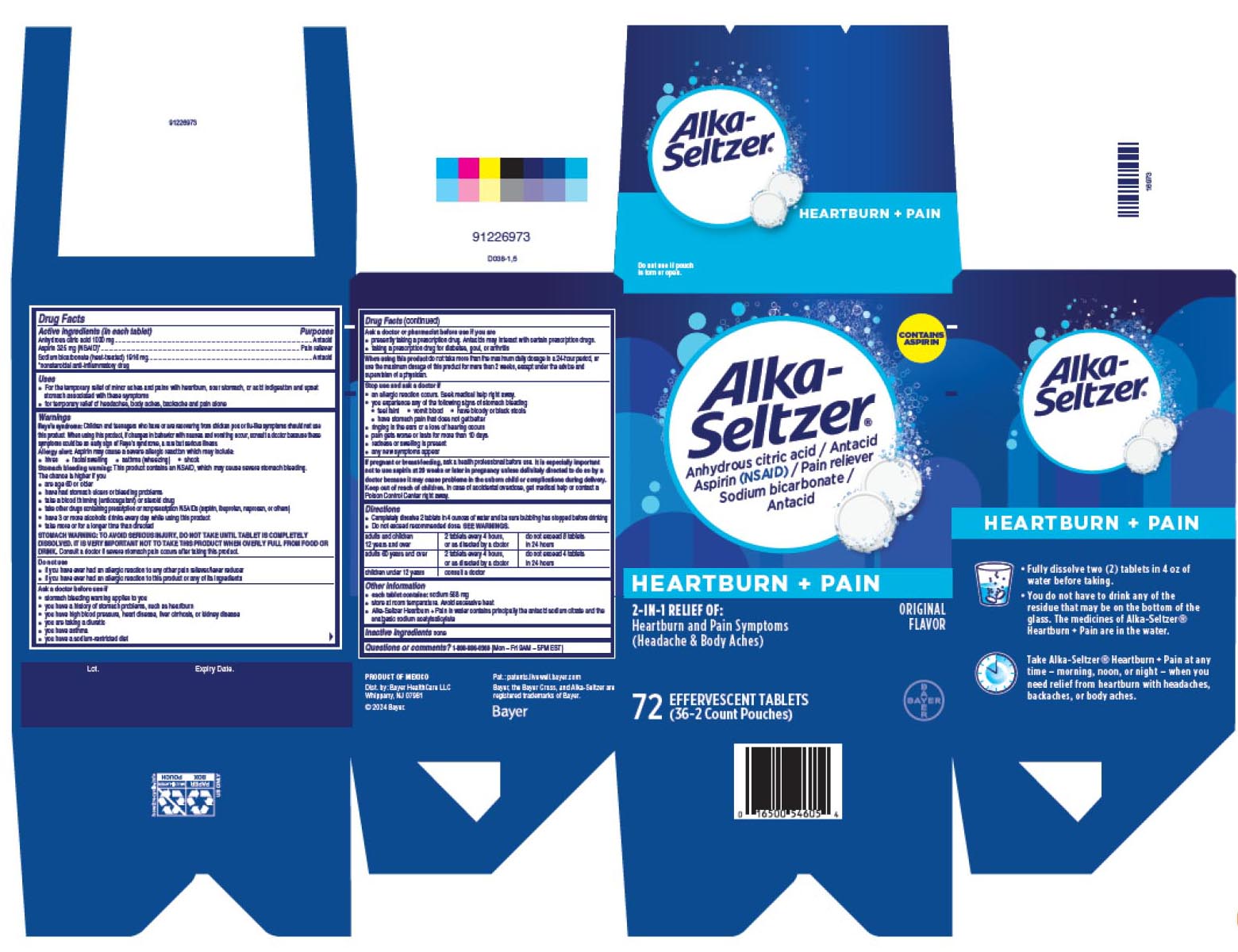 DRUG LABEL: Alka-Seltzer Heartburn and Pain
NDC: 0280-0160 | Form: TABLET, EFFERVESCENT
Manufacturer: Bayer HealthCare LLC.
Category: otc | Type: HUMAN OTC DRUG LABEL
Date: 20241213

ACTIVE INGREDIENTS: ANHYDROUS CITRIC ACID 1000 mg/1 1; ASPIRIN 325 mg/1 1; SODIUM BICARBONATE 1916 mg/1 1

Alka-Seltzer® Heartburn + Pain UI1600130

Drug Facts

ACTIVE INGREDIENT

Active ingredients (in each tablet) | Purpose
Anhydrous citric acid 1000 mg | Antacid
Aspirin 325 mg (NSAID) [nonsteroidal anti-inflammatory drug] | Analgesic
Sodium bicarbonate (heat-treated) 1916 mg | Antacid

Uses

- For the temporary relief of minor aches and pains with heartburn, sour stomach, or acid indigestion and upset stomach associated with these symptoms
- for temporary relief of headaches, body aches, backache and pain alone

Warnings

Reye's syndrome

Children and teenagers who have or are recovering from chicken pox or flu-like symptoms should not use this product. When using this product, if changes in behavior with nausea and vomiting occur, consult a doctor because these symptoms could be an early sign of Reye's syndrome, a rare but serious illness.

Allergy alert

Aspirin may cause a severe allergic reaction which may include:

- hives
- facial swelling
- asthma (wheezing)
- shock

Stomach bleeding warning

This product contains an NSAID, which may cause severe stomach bleeding. The chance is higher if you

- are age 60 or older
- have had stomach ulcers or bleeding problems
- take a blood thinning (anticoagulant) or steroid drug
- take other drugs containing prescription or nonprescription NSAIDs (aspirin, ibuprofen, naproxen, or others)
- have 3 or more alcoholic drinks every day while using this product
- take more or for a longer time than directed

STOMACH WARNING: TO AVOID SERIOUS INJURY, DO NOT TAKE UNTIL TABLET IS COMPLETELY DISSOLVED. IT IS VERY IMPORTANT NOT TO TAKE THIS PRODUCT WHEN OVERLY FULL FROM FOOD OR DRINK. Consult a doctor if severe stomach pain occurs after taking this product.

Do not use

- if you have ever had an allergic reaction to any other pain reliever/fever reducer
- if you have ever had an allergic reaction to this product or any of its ingredients

Ask a doctor before use if

- stomach bleeding warning applies to you
- you have a history of stomach problems, such as heartburn
- you have high blood pressure, heart disease, liver cirrhosis, or kidney disease
- you are taking a diuretic
- you have asthma
- you have a sodium-restricted diet

Ask a doctor or pharmacist before use if you are

- presently taking a prescription drug. Antacids may interact with certain prescription drugs.
- taking a prescription drug for diabetes, gout, or arthritis

When using this product do not take more than the maximum daily dosage in a 24-hour period, or use the maximum dosage of this product for more than 2 weeks, except under the advice and supervision of a physician.

Stop use and ask a doctor if

- an allergic reaction occurs. Seek medical help right away.
- you experience any of the following signs of stomach bleeding
  - feel faint
  - vomit blood
  - have bloody or black stools
  - have stomach pain that does not get better
- ringing in the ears or a loss of hearing occurs
- pain get worse or last more than 10 days
- redness or swelling is present
- any new symptoms appear

PREGNANCY OR BREAST FEEDING

If pregnant or breast-feeding, ask a health professional before use. It is especially important not to use aspirin at 20 weeks or later in pregnancy unless definitely directed to do so by a doctor because it may cause problems in the unborn child or complications during delivery.

Keep out of reach of children. In case of accidental overdose, get medical help or contact a Poison Control Center right away.

Directions

● Completely dissolve 2 tablets in 4 ounces of water and be sure bubbling has stopped before drinking

● Do not exceed recommended dose. SEE WARNINGS

adults and children 12 years and over | 2 tablets every 4 hours, or as directed by a doctor | do not exceed 8 tablets in 24 hours
adults 60 years and over | 2 tablets every 4 hours, or as directed by a doctor | do not exceed 4 tablets in 24 hours
children under 12 years | consult a doctor

Other information

- each tablet contains: sodium 568 mg
- store at room temperature. Avoid excessive heat.
- Alka-Seltzer Heartburn + Pain in water contains principally the antacid sodium citrate and the analgesic sodium acetylsalicylate

Inactive ingredients

none

Questions or comments?

1-800-986-0369 (Mon – Fri 9AM – 5PM EST)

Dist. by: Bayer HealthCare LLC
Whippany, NJ 07981